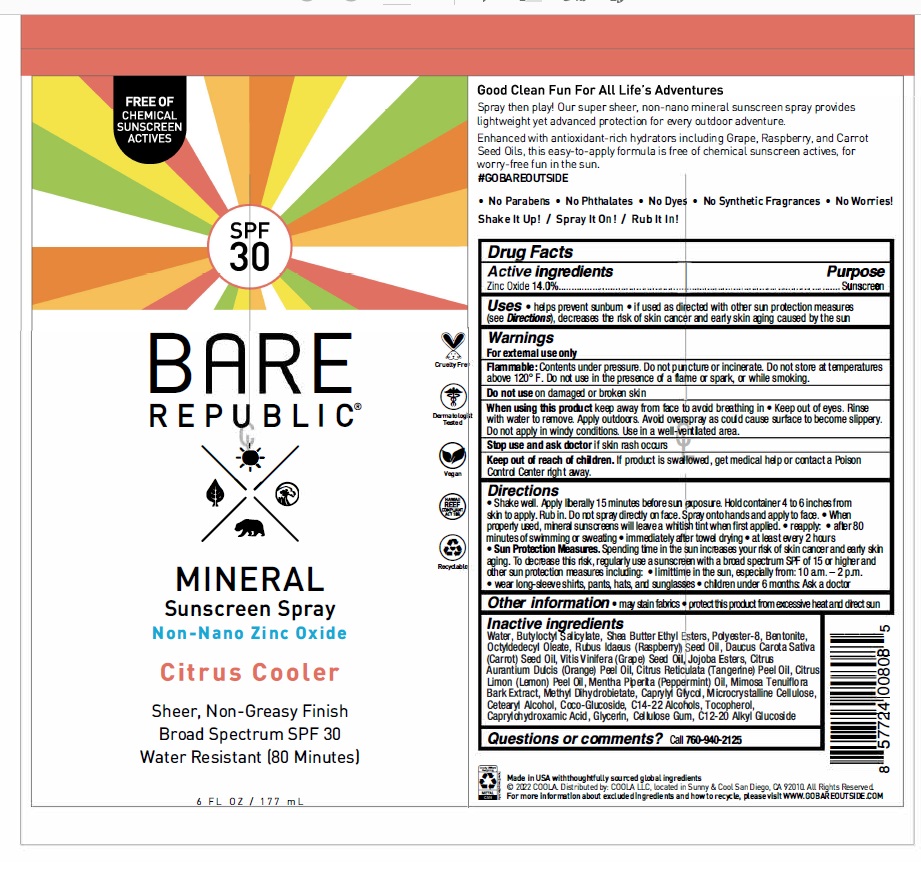 DRUG LABEL: Bare Republic SPF 30 Mineral Sunscreen Citrus Cooler
NDC: 79753-051 | Form: SPRAY
Manufacturer: COOLA, LLC
Category: otc | Type: HUMAN OTC DRUG LABEL
Date: 20240522

ACTIVE INGREDIENTS: ZINC OXIDE 14 g/100 mL
INACTIVE INGREDIENTS: LEMON OIL, COLD PRESSED; PEPPERMINT OIL; WATER; TOCOPHEROL; HYDROGENATED JOJOBA OIL, RANDOMIZED; CAPRYLHYDROXAMIC ACID; POLYESTER-8 (1400 MW, CYANODIPHENYLPROPENOYL CAPPED); CARROT SEED OIL; CETOSTEARYL ALCOHOL; GRAPE SEED OIL; BUTYLOCTYL SALICYLATE; METHYL DIHYDROABIETATE; MICROCRYSTALLINE CELLULOSE; CARBOXYMETHYLCELLULOSE SODIUM, UNSPECIFIED FORM; BENTONITE; RASPBERRY SEED OIL; COCO GLUCOSIDE; SHEA BUTTER ETHYL ESTERS; GLYCERIN; C14-22 ALCOHOLS; OCTYLDODECYL OLEATE; CAPRYLYL GLYCOL; C12-20 ALKYL GLUCOSIDE; MANDARIN OIL; ORANGE OIL, COLD PRESSED; MIMOSA TENUIFLORA BARK

Bare Republic Mineral Spray SPF 30 - Citrus Cooler

ACTIVE INGREDIENT

Zinc Oxide - 14.0%

PURPOSE

Sunscreen

Uses

• Helps prevent sunburn
• If used as directed with other sun protection measures (see Directions), decreases the risk of skin cancer and early skin aging caused by the sun.

WARNINGS

- For external use only
- Flammable: Contents under pressure. Do not puncture or incinerate. Do not store at temperatures above 120° F. Do not use in the presence of a flame or spark, or while smoking.
- Do not use on damaged or broken skin
- When using this product keep away from face to avoid breathing in • Keep out of eyes. Rinse with water to remove. Apply outdoors. Avoid overspray as could cause surface to become slippery. Do not apply in windy conditions. Use in a well ventilated area.
- Stop use and ask doctor if skin rash occurs

Keep out of reach of children. If product is swallowed, get medical help or contact a Poison Control Center right away.

Directions

• Shake well. Apply liberally 15 minutes before sun exposure. Hold container 4 to 6 inches from skin to apply. Rub in. Do not spray directly on face. Spray onto hands and apply to face. • When properly used, mineral sunscreens will leave a whitish tint when first applied.

• Reapply: • after 80 minutes of swimming or sweating • immediately afrer towel drying • at least every 2 hours
• Sun Protection Measures. Spending time in the sun increases your risk of skin cancer and early skin aging. To decrease this risk, regularly use a sunscreen with a broad spectrum SPF of 15 or higher and other sun protection measures including: • limit time in the sun, especially from: 10 a.m. -2 p.m. • wear long-sleeve shirts, pants, hats, and sunglasses

• Children under 6 months: Ask a doctor

OTHER SAFETY INFORMATION

- May stain fabrics
- Protect this product from excessive heat and direct sun

INACTIVE INGREDIENT

Water, Butyloctyl Salicylate, Shea Butter Ethyl Esters, Polyester-8, Bentonite, Octyldodecyl Oleate, Rubus ldaeus (Raspberry) Seed Oil, Daucus Carota Sativa (Carrot) Seed Oil, Vitis Vinifera (Grape) Seed Oil, Jojoba Esters, Citrus Aurantium Dulcis (Orange) Peel Oil, Citrus Reticulata (Tangerine) Peel Oil, Citrus Limon (Lemon) Peel Oil, Mentha Piperita (Peppermint) Oil, Mimosa Tenuiflora Bark Extract, Me1hyl Dihydrobietate, Caprylyl Glycol, Microcrystalline Cellulose, Cetearyl Alcohol, Coco-Glucoside, C14-22 Alcohols, Tocopherol, Caprylohydroxamic Acid, Glycerin, Cellulose Gum, C12-20 Alkyl Glucoside

QUESTIONS

Call 760-940-2125